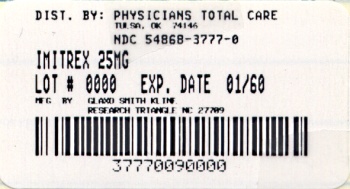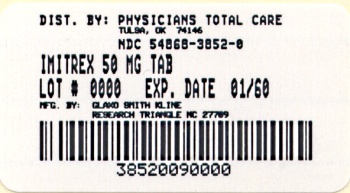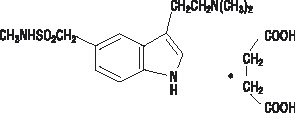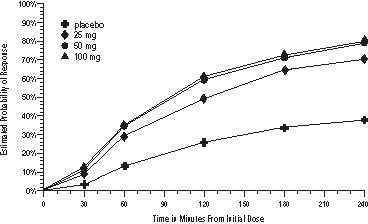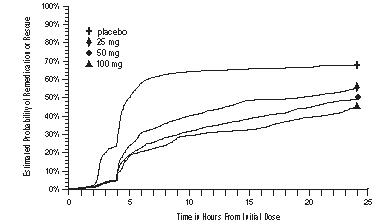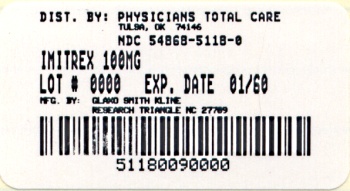 DRUG LABEL: IMITREX
NDC: 54868-3777 | Form: TABLET, FILM COATED
Manufacturer: Physicians Total Care, Inc.
Category: prescription | Type: HUMAN PRESCRIPTION DRUG LABEL
Date: 20121002

ACTIVE INGREDIENTS: SUMATRIPTAN SUCCINATE 25 mg/1 1
INACTIVE INGREDIENTS: CROSCARMELLOSE SODIUM; CALCIUM PHOSPHATE, DIBASIC, ANHYDROUS; MAGNESIUM STEARATE; CELLULOSE, MICROCRYSTALLINE; SODIUM BICARBONATE

IMITREX®
(sumatriptansuccinate)
Tablets

DESCRIPTION

IMITREX Tablets contain sumatriptan (as the succinate), a selective 5-hydroxytryptamine1 receptor subtype agonist. Sumatriptan succinate is chemically designated as 3-[2-(dimethylamino)ethyl]-N-methyl-indole-5-methanesulfonamide succinate (1:1), and it has the following structure:

The empirical formula is C14H21N3O2S•C4H6O4, representing a molecular weight of 413.5. Sumatriptan succinate is a white to off-white powder that is readily soluble in water and in saline. Each IMITREX Tablet for oral administration contains 35, 70, or 140 mg of sumatriptan succinate equivalent to 25, 50, or 100 mg of sumatriptan, respectively. Each tablet also contains the inactive ingredients croscarmellose sodium, dibasic calcium phosphate, magnesium stearate, microcrystalline cellulose, and sodium bicarbonate. Each 100-mg tablet also contains hypromellose, iron oxide, titanium dioxide, and triacetin.

CLINICAL PHARMACOLOGY

Mechanism of Action

Sumatriptan is an agonist for a vascular 5‑hydroxytryptamine1 receptor subtype (probably a member of the 5‑HT1D family) having only a weak affinity for 5‑HT1A, 5‑HT5A, and 5‑HT7 receptors and no significant affinity (as measured using standard radioligand binding assays) or pharmacological activity at 5‑HT2, 5‑HT3, or 5‑HT4 receptor subtypes or at alpha1‑, alpha2‑, or beta‑adrenergic; dopamine1; dopamine2; muscarinic; or benzodiazepine receptors.

The vascular 5‑HT1 receptor subtype that sumatriptan activates is present on cranial arteries in both dog and primate, on the human basilar artery, and in the vasculature of human dura mater and mediates vasoconstriction. This action in humans correlates with the relief of migraine headache. In addition to causing vasoconstriction, experimental data from animal studies show that sumatriptan also activates 5‑HT1 receptors on peripheral terminals of the trigeminal nerve innervating cranial blood vessels. Such an action may also contribute to the antimigrainous effect of sumatriptan in humans.

In the anesthetized dog, sumatriptan selectively reduces the carotid arterial blood flow with little or no effect on arterial blood pressure or total peripheral resistance. In the cat, sumatriptan selectively constricts the carotid arteriovenous anastomoses while having little effect on blood flow or resistance in cerebral or extracerebral tissues.

Pharmacokinetics

The mean maximum concentration following oral dosing with 25 mg is 18 ng/mL (range: 7 to 47 ng/mL) and 51 ng/mL (range: 28 to 100 ng/mL) following oral dosing with 100 mg of sumatriptan. This compares with a Cmax of 5 and 16 ng/mL following dosing with a 5- and 20‑mg intranasal dose, respectively. The mean Cmax following a 6‑mg subcutaneous injection is 71 ng/mL (range: 49 to 110 ng/mL). The bioavailability is approximately 15%, primarily due to presystemic metabolism and partly due to incomplete absorption. The Cmax is similar during a migraine attack and during a migraine‑free period, but the Tmax is slightly later during the attack, approximately 2.5 hours compared to 2.0 hours. When given as a single dose, sumatriptan displays dose proportionality in its extent of absorption (area under the curve [AUC]) over the dose range of 25 to 200 mg, but the Cmax after 100 mg is approximately 25% less than expected (based on the 25‑mg dose).

A food effect study involving administration of IMITREX Tablets 100 mg to healthy volunteers under fasting conditions and with a high‑fat meal indicated that the Cmax and AUC were increased by 15% and 12%, respectively, when administered in the fed state.

Plasma protein binding is low (14% to 21%). The effect of sumatriptan on the protein binding of other drugs has not been evaluated, but would be expected to be minor, given the low rate of protein binding. The apparent volume of distribution is 2.4 L/kg.

The elimination half‑life of sumatriptan is approximately 2.5 hours. Radiolabeled ^14C‑sumatriptan administered orally is largely renally excreted (about 60%) with about 40% found in the feces. Most of the radiolabeled compound excreted in the urine is the major metabolite, indole acetic acid (IAA), which is inactive, or the IAA glucuronide. Only 3% of the dose can be recovered as unchanged sumatriptan.

In vitro studies with human microsomes suggest that sumatriptan is metabolized by monoamine oxidase (MAO), predominantly the A isoenzyme, and inhibitors of that enzyme may alter sumatriptan pharmacokinetics to increase systemic exposure. No significant effect was seen with an MAO‑B inhibitor (see CONTRAINDICATIONS, WARNINGS, and PRECAUTIONS: Drug Interactions).

Special Populations

Renal Impairment: The effect of renal impairment on the pharmacokinetics of sumatriptan has not been examined, but little clinical effect would be expected as sumatriptan is largely metabolized to an inactive substance.

Hepatic Impairment: The liver plays an important role in the presystemic clearance of orally administered sumatriptan. Accordingly, the bioavailability of sumatriptan following oral administration may be markedly increased in patients with liver disease. In 1 small study of hepatically impaired patients (N = 8) matched for sex, age, and weight with healthy subjects, the hepatically impaired patients had an approximately 70% increase in AUC and Cmax and a Tmax 40 minutes earlier compared to the healthy subjects (see DOSAGE AND ADMINISTRATION).

Age: The pharmacokinetics of oral sumatriptan in the elderly (mean age: 72 years, 2 males and 4 females) and in patients with migraine (mean age: 38 years, 25 males and 155 females) were similar to that in healthy male subjects (mean age: 30 years) (see PRECAUTIONS: Geriatric Use).

Gender: In a study comparing females to males, no pharmacokinetic differences were observed between genders for AUC, Cmax, Tmax, and half‑life.

Race: The systemic clearance and Cmax of sumatriptan were similar in black (N = 34) and Caucasian (N = 38) healthy male subjects.

Drug Interactions

Monoamine Oxidase Inhibitors: Treatment with MAO-A inhibitors generally leads to an increase of sumatriptan plasma levels (see CONTRAINDICATIONS and PRECAUTIONS).

Due to gut and hepatic metabolic first-pass effects, the increase of systemic exposure after coadministration of an MAO-A inhibitor with oral sumatriptan is greater than after coadministration of the monoamine oxidase inhibitors (MAOI) with subcutaneous sumatriptan. In a study of 14 healthy females, pretreatment with an MAO-A inhibitor decreased the clearance of subcutaneous sumatriptan. Under the conditions of this experiment, the result was a 2-fold increase in the area under the sumatriptan plasma concentration × time curve (AUC), corresponding to a 40% increase in elimination half-life. This interaction was not evident with an MAO-B inhibitor.

A small study evaluating the effect of pretreatment with an MAO-A inhibitor on the bioavailability from a 25-mg oral sumatriptan tablet resulted in an approximately 7-fold increase in systemic exposure.

Alcohol: Alcohol consumed 30 minutes prior to sumatriptan ingestion had no effect on the pharmacokinetics of sumatriptan.

CLINICAL STUDIES

The efficacy of IMITREX Tablets in the acute treatment of migraine headaches was demonstrated in 3, randomized, double-blind, placebo-controlled studies. Patients enrolled in these 3 studies were predominately female (87%) and Caucasian (97%), with a mean age of 40 years (range, 18 to 65 years). Patients were instructed to treat a moderate to severe headache. Headache response, defined as a reduction in headache severity from moderate or severe pain to mild or no pain, was assessed up to 4 hours after dosing. Associated symptoms such as nausea, photophobia, and phonophobia were also assessed. Maintenance of response was assessed for up to 24 hours postdose. A second dose of IMITREX Tablets or other medication was allowed 4 to 24 hours after the initial treatment for recurrent headache. Acetaminophen was offered to patients in Studies 2 and 3 beginning at 2 hours after initial treatment if the migraine pain had not improved or worsened. Additional medications were allowed 4 to 24 hours after the initial treatment for recurrent headache or as rescue in all 3 studies. The frequency and time to use of these additional treatments were also determined. In all studies, doses of 25, 50, and 100 mg were compared to placebo in the treatment of migraine attacks. In 1 study, doses of 25, 50, and 100 mg were also compared to each other.

In all 3 trials, the percentage of patients achieving headache response 2 and 4 hours after treatment was significantly greater among patients receiving IMITREX Tablets at all doses compared to those who received placebo. In 1 of the 3 studies, there was a statistically significant greater percentage of patients with headache response at 2 and 4 hours in the 50- or 100-mg group when compared to the 25-mg dose groups. There were no statistically significant differences between the 50- and 100-mg dose groups in any study. The results from the 3 controlled clinical trials are summarized in Table 1.

Comparisons of drug performance based upon results obtained in different clinical trials are never reliable. Because studies are conducted at different times, with different samples of patients, by different investigators, employing different criteria and/or different interpretations of the same criteria, under different conditions (dose, dosing regimen, etc.), quantitative estimates of treatment response and the timing of response may be expected to vary considerably from study to study.

Table 1. Percentage of Patients With Headache Response (No or Mild Pain) 2 and 4 Hours Following Treatment
 | Placebo; 2 hr 4 hr | IMITREX Tablets; 25 mg; 2 hr 4 hr | IMITREX Tablets; 50 mg; 2 hr 4 hr | IMITREX Tablets; 100 mg; 2 hr 4 hr
Study 1 | 27% 38% | 52%a 67%a | 61%ab 78%ab | 62%ab 79%ab
 | (N = 94) | (N = 298) | (N = 296) | (N = 296)
Study 2 | 26% 38% | 52%a 70%a | 50%a 68%a | 56%a 71%a
 | (N = 65) | (N = 66) | (N = 62) | (N = 66)
Study 3 | 17% 19% | 52%a 65%a | 54%a 72%a | 57%a 78%a
 | (N = 47) | (N = 48) | (N = 46) | (N = 46)

a P<0.05 in comparison with placebo.

b P<0.05 in comparison with 25 mg.

The estimated probability of achieving an initial headache response over the 4 hours following treatment is depicted in Figure 1.

Figure 1. Estimated Probability of Achieving Initial Headache Response Within 240 Minutesa

aThe figure shows the probability over time of obtaining headache response (no or mild pain) following treatment with sumatriptan. The averages displayed are based on pooled data from the 3 clinical controlled trials providing evidence of efficacy. Kaplan-Meier plot with patients not achieving response and/or taking rescue within 240 minutes censored to 240 minutes.

For patients with migraine-associated nausea, photophobia, and/or phonophobia at baseline, there was a lower incidence of these symptoms at 2 hours (Study 1) and at 4 hours (Studies 1, 2, and 3) following administration of IMITREX Tablets compared to placebo.

As early as 2 hours in Studies 2 and 3 or 4 hours in Study 1, through 24 hours following the initial dose of study treatment, patients were allowed to use additional treatment for pain relief in the form of a second dose of study treatment or other medication. The estimated probability of patients taking a second dose or other medication for migraine over the 24 hours following the initial dose of study treatment is summarized in Figure 2.

Figure 2. The Estimated Probability of Patients Taking a Second Dose or Other Medication for Migraine Over the 24 Hours Following the Initial Dose of Study Treatmenta

aKaplan-Meier plot based on data obtained in the 3 clinical controlled trials providing evidence of efficacy with patients not using additional treatments censored to 24 hours. Plot also includes patients who had no response to the initial dose. No remedication was allowed within 2 hours postdose.

There is evidence that doses above 50 mg do not provide a greater effect than 50 mg. There was no evidence to suggest that treatment with sumatriptan was associated with an increase in the severity of recurrent headaches. The efficacy of IMITREX Tablets was unaffected by presence of aura; duration of headache prior to treatment; gender, age, or weight of the patient; relationship to menses; or concomitant use of common migraine prophylactic drugs (e.g., beta-blockers, calcium channel blockers, tricyclic antidepressants). There were insufficient data to assess the impact of race on efficacy.

INDICATIONS AND USAGE

IMITREX Tablets are indicated for the acute treatment of migraine attacks with or without aura in adults.

IMITREX Tablets are not intended for the prophylactic therapy of migraine or for use in the management of hemiplegic or basilar migraine (see CONTRAINDICATIONS). Safety and effectiveness of IMITREX Tablets have not been established for cluster headache, which is present in an older, predominantly male population.

CONTRAINDICATIONS

IMITREX Tablets should not be given to patients with history, symptoms, or signs of ischemic cardiac, cerebrovascular, or peripheral vascular syndromes. In addition, patients with other significant underlying cardiovascular diseases should not receive IMITREX Tablets. Ischemic cardiac syndromes include, but are not limited to, angina pectoris of any type (e.g., stable angina of effort, vasospastic forms of angina such as the Prinzmetal variant), all forms of myocardial infarction, and silent myocardial ischemia. Cerebrovascular syndromes include, but are not limited to, strokes of any type as well as transient ischemic attacks. Peripheral vascular disease includes, but is not limited to, ischemic bowel disease (see WARNINGS).

Because IMITREX Tablets may increase blood pressure, they should not be given to patients with uncontrolled hypertension.

Concurrent administration of MAO-A inhibitors or use within 2 weeks of discontinuation of MAO-A inhibitor therapy is contraindicated (see CLINICAL PHARMACOLOGY: Drug Interactions and PRECAUTIONS: Drug Interactions).

IMITREX Tablets should not be administered to patients with hemiplegic or basilar migraine.

IMITREX Tablets and any ergotamine-containing or ergot-type medication (like dihydroergotamine or methysergide) should not be used within 24 hours of each other, nor should IMITREX and another 5-HT1 agonist.

IMITREX Tablets are contraindicated in patients with hypersensitivity to sumatriptan or any of their components.

IMITREX Tablets are contraindicated in patients with severe hepatic impairment.

WARNINGS

IMITREX Tablets should only be used where a clear diagnosis of migraine headache has been established.

Risk of Myocardial Ischemia and/or Infarction and Other Adverse Cardiac Events

Sumatriptan should not be given to patients with documented ischemic or vasospastic coronary artery disease (CAD) (see CONTRAINDICATIONS). It is strongly recommended that sumatriptan not be given to patients in whom unrecognized CAD is predicted by the presence of risk factors (e.g., hypertension, hypercholesterolemia, smoker, obesity, diabetes, strong family history of CAD, female with surgical or physiological menopause, male over 40 years of age) unless a cardiovascular evaluation provides satisfactory clinical evidence that the patient is reasonably free of coronary artery and ischemic myocardial disease or other significant underlying cardiovascular disease. The sensitivity of cardiac diagnostic procedures to detect cardiovascular disease or predisposition to coronary artery vasospasm is modest, at best. If, during the cardiovascular evaluation, the patient’s medical history or electrocardiographic investigations reveal findings indicative of, or consistent with, coronary artery vasospasm or myocardial ischemia, sumatriptan should not be administered (see CONTRAINDICATIONS).

For patients with risk factors predictive of CAD, who are determined to have a satisfactory cardiovascular evaluation, it is strongly recommended that administration of the first dose of sumatriptan tablets take place in the setting of a physician’s office or similar medically staffed and equipped facility unless the patient has previously received sumatriptan. Because cardiac ischemia can occur in the absence of clinical symptoms, consideration should be given to obtaining on the first occasion of use an electrocardiogram (ECG) during the interval immediately following IMITREX Tablets in these patients with risk factors.

It is recommended that patients who are intermittent long-term users of sumatriptan and who have or acquire risk factors predictive of CAD, as described above, undergo periodic interval cardiovascular evaluation as they continue to use sumatriptan.

The systematic approach described above is intended to reduce the likelihood that patients with unrecognized cardiovascular disease will be inadvertently exposed to sumatriptan.

Drug-Associated Cardiac Events and Fatalities

Serious adverse cardiac events, including acute myocardial infarction, life-threatening disturbances of cardiac rhythm, and death have been reported within a few hours following the administration of IMITREX® (sumatriptan succinate) Injection or IMITREX Tablets. Considering the extent of use of sumatriptan in patients with migraine, the incidence of these events is extremely low.

The fact that sumatriptan can cause coronary vasospasm, that some of these events have occurred in patients with no prior cardiac disease history and with documented absence of CAD, and the close proximity of the events to sumatriptan use support the conclusion that some of these cases were caused by the drug. In many cases, however, where there has been known underlying coronary artery disease, the relationship is uncertain.

Premarketing Experience With Sumatriptan: Of 6,348 patients with migraine who participated in premarketing controlled and uncontrolled clinical trials of oral sumatriptan, 2 experienced clinical adverse events shortly after receiving oral sumatriptan that may have reflected coronary vasospasm. Neither of these adverse events was associated with a serious clinical outcome.

Among the more than 1,900 patients with migraine who participated in premarketing controlled clinical trials of subcutaneous sumatriptan, there were 8 patients who sustained clinical events during or shortly after receiving sumatriptan that may have reflected coronary artery vasospasm. Six of these 8 patients had ECG changes consistent with transient ischemia, but without accompanying clinical symptoms or signs. Of these 8 patients, 4 had either findings suggestive of CAD or risk factors predictive of CAD prior to study enrollment.

Among approximately 4,000 patients with migraine who participated in premarketing controlled and uncontrolled clinical trials of sumatriptan nasal spray, 1 patient experienced an asymptomatic subendocardial infarction possibly subsequent to a coronary vasospastic event.

Postmarketing Experience With Sumatriptan: Serious cardiovascular events, some resulting in death, have been reported in association with the use of IMITREX Injection or IMITREX Tablets. The uncontrolled nature of postmarketing surveillance, however, makes it impossible to determine definitively the proportion of the reported cases that were actually caused by sumatriptan or to reliably assess causation in individual cases. On clinical grounds, the longer the latency between the administration of IMITREX and the onset of the clinical event, the less likely the association is to be causative. Accordingly, interest has focused on events beginning within 1 hour of the administration of IMITREX.

Cardiac events that have been observed to have onset within 1 hour of sumatriptan administration include: coronary artery vasospasm, transient ischemia, myocardial infarction, ventricular tachycardia and ventricular fibrillation, cardiac arrest, and death.

Some of these events occurred in patients who had no findings of CAD and appear to represent consequences of coronary artery vasospasm. However, among domestic reports of serious cardiac events within 1 hour of sumatriptan administration, almost all of the patients had risk factors predictive of CAD and the presence of significant underlying CAD was established in most cases (see CONTRAINDICATIONS).

Drug-Associated Cerebrovascular Events and Fatalities

Cerebral hemorrhage, subarachnoid hemorrhage, stroke, and other cerebrovascular events have been reported in patients treated with oral or subcutaneous sumatriptan, and some have resulted in fatalities. The relationship of sumatriptan to these events is uncertain. In a number of cases, it appears possible that the cerebrovascular events were primary, sumatriptan having been administered in the incorrect belief that the symptoms experienced were a consequence of migraine when they were not. As with other acute migraine therapies, before treating headaches in patients not previously diagnosed as migraineurs, and in migraineurs who present with atypical symptoms, care should be taken to exclude other potentially serious neurological conditions. It should also be noted that patients with migraine may be at increased risk of certain cerebrovascular events (e.g., cerebrovascular accident, transient ischemic attack).

Other Vasospasm-Related Events

Sumatriptan may cause vasospastic reactions other than coronary artery vasospasm. Both peripheral vascular ischemia and colonic ischemia with abdominal pain and bloody diarrhea have been reported. Very rare reports of transient and permanent blindness and significant partial vision loss have been reported with the use of sumatriptan. Visual disorders may also be part of a migraine attack.

Serotonin Syndrome

Serotonin syndrome may occur with triptans, including IMITREX, particularly during combined use with selective serotonin reuptake inhibitors (SSRIs) or serotonin norepinephrine reuptake inhibitors (SNRIs). Serotonin syndrome symptoms may include mental status changes (e.g., agitation, hallucinations, coma), autonomic instability (e.g., tachycardia, labile blood pressure, hyperthermia), neuromuscular aberrations (e.g., hyperreflexia, incoordination), and/or gastrointestinal symptoms (e.g., nausea, vomiting, diarrhea). The onset of symptoms can occur within minutes to hours of receiving a new or a greater dose of a serotonergic medication. Treatment with IMITREX should be discontinued if serotonin syndrome is suspected.

Increase in Blood Pressure

Significant elevation in blood pressure, including hypertensive crisis, has been reported on rare occasions in patients with and without a history of hypertension. Sumatriptan is contraindicated in patients with uncontrolled hypertension (see CONTRAINDICATIONS). Sumatriptan should be administered with caution to patients with controlled hypertension as transient increases in blood pressure and peripheral vascular resistance have been observed in a small proportion of patients.

Concomitant Drug Use

In patients taking MAO-A inhibitors, sumatriptan plasma levels attained after treatment with recommended doses are 7-fold higher following oral administration than those obtained under other conditions. Accordingly, the coadministration of IMITREX Tablets and an MAO-A inhibitor is contraindicated (see CLINICAL PHARMACOLOGY and CONTRAINDICATIONS).

Hypersensitivity

Hypersensitivity (anaphylaxis/anaphylactoid) reactions have occurred on rare occasions in patients receiving sumatriptan. Such reactions can be life threatening or fatal. In general, hypersensitivity reactions to drugs are more likely to occur in individuals with a history of sensitivity to multiple allergens (see CONTRAINDICATIONS).

PRECAUTIONS

General

Chest discomfort and jaw or neck tightness have been reported following use of IMITREX Tablets and have also been reported infrequently following administration of IMITREX® (sumatriptan) Nasal Spray. Chest, jaw, or neck tightness is relatively common after administration of IMITREX Injection. Only rarely have these symptoms been associated with ischemic ECG changes. However, because sumatriptan may cause coronary artery vasospasm, patients who experience signs or symptoms suggestive of angina following sumatriptan should be evaluated for the presence of CAD or a predisposition to Prinzmetal variant angina before receiving additional doses of sumatriptan, and should be monitored electrocardiographically if dosing is resumed and similar symptoms recur. Similarly, patients who experience other symptoms or signs suggestive of decreased arterial flow, such as ischemic bowel syndrome or Raynaud syndrome following sumatriptan should be evaluated for atherosclerosis or predisposition to vasospasm (see WARNINGS).

IMITREX should also be administered with caution to patients with diseases that may alter the absorption, metabolism, or excretion of drugs, such as impaired hepatic or renal function.

There have been rare reports of seizure following administration of sumatriptan. Sumatriptan should be used with caution in patients with a history of epilepsy or conditions associated with a lowered seizure threshold.

Care should be taken to exclude other potentially serious neurologic conditions before treating headache in patients not previously diagnosed with migraine headache or who experience a headache that is atypical for them. There have been rare reports where patients received sumatriptan for severe headaches that were subsequently shown to have been secondary to an evolving neurologic lesion (see WARNINGS).

For a given attack, if a patient does not respond to the first dose of sumatriptan, the diagnosis of migraine should be reconsidered before administration of a second dose.

Overuse

Overuse of acute migraine drugs (e.g., ergotamine, triptans, opioids, or a combination of drugs for 10 or more days per month) may lead to exacerbation of headache (medication overuse headache). Medication overuse headache may present as migraine-like daily headaches, or as a marked increase in frequency of migraine attacks. Detoxification of patients, including withdrawal of the overused drugs, and treatment of withdrawal symptoms (which often includes a transient worsening of headache) may be necessary. Migraine patients should be informed about the risks of medication overuse and encouraged to record headache frequency and drug use.

Information for Patients

See PATIENT INFORMATION at the end of this labeling for the text of the separate leaflet provided for patients.

Patients should be cautioned about the risk of serotonin syndrome with the use of sumatriptan or other triptans, especially during combined use with SSRIs or SNRIs.

Laboratory Tests

No specific laboratory tests are recommended for monitoring patients prior to and/or after treatment with sumatriptan.

Drug Interactions

Selective Serotonin Reuptake Inhibitors/Serotonin Norepinephrine Reuptake Inhibitors and Serotonin Syndrome: Cases of life-threatening serotonin syndrome have been reported during combined use of SSRIs or SNRIs and triptans (see WARNINGS).

Ergot-Containing Drugs: Ergot-containing drugs have been reported to cause prolonged vasospastic reactions. Because there is a theoretical basis that these effects may be additive, use of ergotamine-containing or ergot-type medications (like dihydroergotamine or methysergide) and sumatriptan within 24 hours of each other should be avoided (see CONTRAINDICATIONS).

Monoamine Oxidase-A Inhibitors: MAO-A inhibitors reduce sumatriptan clearance, significantly increasing systemic exposure. Therefore, the use of IMITREX Tablets in patients receiving MAO-A inhibitors is contraindicated (see CLINICAL PHARMACOLOGY and CONTRAINDICATIONS).

Drug/Laboratory Test Interactions

IMITREX Tablets are not known to interfere with commonly employed clinical laboratory tests.

Carcinogenesis, Mutagenesis, Impairment of Fertility

Carcinogenesis: In carcinogenicity studies, rats and mice were given sumatriptan by oral gavage (rats: 104 weeks) or drinking water (mice: 78 weeks). Average exposures achieved in mice receiving the highest dose (target dose of 160 mg/kg/day) were approximately 40 times the exposure attained in humans after the maximum recommended single oral dose of 100 mg. The highest dose administered to rats (160 mg/kg/day, reduced from 360 mg/kg/day during week 21) was approximately 15 times the maximum recommended single human oral dose of 100 mg on a mg/m^2 basis. There was no evidence of an increase in tumors in either species related to sumatriptan administration.

Mutagenesis: Sumatriptan was not mutagenic in the presence or absence of metabolic activation when tested in 2 gene mutation assays (the Ames test and the in vitro mammalian Chinese hamster V79/HGPRT assay). In 2 cytogenetics assays (the in vitro human lymphocyte assay and the in vivo rat micronucleus assay) sumatriptan was not associated with clastogenic activity.

Impairment of Fertility: In a study in which male and female rats were dosed daily with oral sumatriptan prior to and throughout the mating period, there was a treatment-related decrease in fertility secondary to a decrease in mating in animals treated with 50 and 500 mg/kg/day. The highest no-effect dose for this finding was 5 mg/kg/day, or approximately one half of the maximum recommended single human oral dose of 100 mg on a mg/m^2 basis. It is not clear whether the problem is associated with treatment of the males or females or both combined. In a similar study by the subcutaneous route there was no evidence of impaired fertility at 60 mg/kg/day, the maximum dose tested, which is equivalent to approximately 6 times the maximum recommended single human oral dose of 100 mg on a mg/m^2 basis.

Pregnancy

Pregnancy Category C. In reproductive toxicity studies in rats and rabbits, oral treatment with sumatriptan was associated with embryolethality, fetal abnormalities, and pup mortality. When administered by the intravenous route to rabbits, sumatriptan has been shown to be embryolethal. There are no adequate and well-controlled studies in pregnant women. Therefore, IMITREX should be used during pregnancy only if the potential benefit justifies the potential risk to the fetus. In assessing this information, the following findings should be considered.

Embryolethality: When given orally or intravenously to pregnant rabbits daily throughout the period of organogenesis, sumatriptan caused embryolethality at doses at or close to those producing maternal toxicity. In the oral studies this dose was 100 mg/kg/day, and in the intravenous studies this dose was 2.0 mg/kg/day. The mechanism of the embryolethality is not known. The highest no-effect dose for embryolethality by the oral route was 50 mg/kg/day, which is approximately 9 times the maximum single recommended human oral dose of 100 mg on a mg/m^2 basis. By the intravenous route, the highest no-effect dose was 0.75 mg/kg/day, or approximately one tenth of the maximum single recommended human oral dose of 100 mg on a mg/m^2 basis.

The intravenous administration of sumatriptan to pregnant rats throughout organogenesis at 12.5 mg/kg/day, the maximum dose tested, did not cause embryolethality. This dose is equivalent to the maximum single recommended human oral dose of 100 mg on a mg/m^2 basis. Additionally, in a study in rats given subcutaneous sumatriptan daily prior to and throughout pregnancy at 60 mg/kg/day, the maximum dose tested, there was no evidence of increased embryo/fetal lethality. This dose is equivalent to approximately 6 times the maximum recommended single human oral dose of 100 mg on a mg/m^2 basis.

Teratogenicity: Oral treatment of pregnant rats with sumatriptan during the period of organogenesis resulted in an increased incidence of blood vessel abnormalities (cervicothoracic and umbilical) at doses of approximately 250 mg/kg/day or higher. The highest no-effect dose was approximately 60 mg/kg/day, which is approximately 6 times the maximum single recommended human oral dose of 100 mg on a mg/m^2 basis. Oral treatment of pregnant rabbits with sumatriptan during the period of organogenesis resulted in an increased incidence of cervicothoracic vascular and skeletal abnormalities. The highest no-effect dose for these effects was 15 mg/kg/day, or approximately 3 times the maximum single recommended human oral dose of 100 mg on a mg/m^2 basis.

A study in which rats were dosed daily with oral sumatriptan prior to and throughout gestation demonstrated embryo/fetal toxicity (decreased body weight, decreased ossification, increased incidence of rib variations) and an increased incidence of a syndrome of malformations (short tail/short body and vertebral disorganization) at 500 mg/kg/day. The highest no-effect dose was 50 mg/kg/day, or approximately 5 times the maximum single recommended human oral dose of 100 mg on a mg/m^2 basis. In a study in rats dosed daily with subcutaneous sumatriptan prior to and throughout pregnancy, at a dose of 60 mg/kg/day, the maximum dose tested, there was no evidence of teratogenicity. This dose is equivalent to approximately 6 times the maximum recommended single human oral dose of 100 mg on a mg/m2 basis.

Pup Deaths: Oral treatment of pregnant rats with sumatriptan during the period of organogenesis resulted in a decrease in pup survival between birth and postnatal day 4 at doses of approximately 250 mg/kg/day or higher. The highest no-effect dose for this effect was approximately 60 mg/kg/day, or 6 times the maximum single recommended human oral dose of 100 mg on a mg/m^2 basis.

Oral treatment of pregnant rats with sumatriptan from gestational day 17 through postnatal day 21 demonstrated a decrease in pup survival measured at postnatal days 2, 4, and 20 at the dose of 1,000 mg/kg/day. The highest no-effect dose for this finding was 100 mg/kg/day, approximately 10 times the maximum single recommended human oral dose of 100 mg on a mg/m^2 basis. In a similar study in rats by the subcutaneous route there was no increase in pup death at 81 mg/kg/day, the highest dose tested, which is equivalent to 8 times the maximum single recommended human oral dose of 100 mg on a mg/m^2 basis.

Nursing Mothers

Sumatriptan is excreted in human breast milk following subcutaneous administration. Infant exposure to sumatriptan can be minimized by avoiding breastfeeding for 12 hours after treatment with IMITREX Tablets.

Pediatric Use

Safety and effectiveness of IMITREX Tablets in pediatric patients under 18 years of age have not been established; therefore, IMITREX Tablets are not recommended for use in patients under 18 years of age.

Two controlled clinical trials evaluating sumatriptan nasal spray (5 to 20 mg) in pediatric patients aged 12 to 17 years enrolled a total of 1,248 adolescent migraineurs who treated a single attack. The studies did not establish the efficacy of sumatriptan nasal spray compared to placebo in the treatment of migraine in adolescents. Adverse events observed in these clinical trials were similar in nature to those reported in clinical trials in adults.

Five controlled clinical trials (2 single attack studies, 3 multiple attack studies) evaluating oral sumatriptan (25 to 100 mg) in pediatric patients aged 12 to 17 years enrolled a total of 701 adolescent migraineurs. These studies did not establish the efficacy of oral sumatriptan compared to placebo in the treatment of migraine in adolescents. Adverse events observed in these clinical trials were similar in nature to those reported in clinical trials in adults. The frequency of all adverse events in these patients appeared to be both dose- and age-dependent, with younger patients reporting events more commonly than older adolescents.

Postmarketing experience documents that serious adverse events have occurred in the pediatric population after use of subcutaneous, oral, and/or intranasal sumatriptan. These reports include events similar in nature to those reported rarely in adults, including stroke, visual loss, and death. A myocardial infarction has been reported in a 14-year-old male following the use of oral sumatriptan; clinical signs occurred within 1 day of drug administration. Since clinical data to determine the frequency of serious adverse events in pediatric patients who might receive injectable, oral, or intranasal sumatriptan are not presently available, the use of sumatriptan in patients aged younger than 18 years is not recommended.

Geriatric Use

The use of sumatriptan in elderly patients is not recommended because elderly patients are more likely to have decreased hepatic function, they are at higher risk for CAD, and blood pressure increases may be more pronounced in the elderly (see WARNINGS).

ADVERSE REACTIONS

Serious cardiac events, including some that have been fatal, have occurred following the use of IMITREX Injection or Tablets. These events are extremely rare and most have been reported in patients with risk factors predictive of CAD. Events reported have included coronary artery vasospasm, transient myocardial ischemia, myocardial infarction, ventricular tachycardia, and ventricular fibrillation (see CONTRAINDICATIONS, WARNINGS, and PRECAUTIONS).

Significant hypertensive episodes, including hypertensive crises, have been reported on rare occasions in patients with or without a history of hypertension (see WARNINGS).

Incidence in Controlled Clinical Trials

Table 2 lists adverse events that occurred in placebo-controlled clinical trials in patients who took at least 1 dose of study drug. Only events that occurred at a frequency of 2% or more in any group treated with IMITREX Tablets and were more frequent in that group than in the placebo group are included in Table 2. The events cited reflect experience gained under closely monitored conditions of clinical trials in a highly selected patient population. In actual clinical practice or in other clinical trials, these frequency estimates may not apply, as the conditions of use, reporting behavior, and the kinds of patients treated may differ.

Table 2. Treatment Emergent Adverse Events Reported by at Least 2% of Patients in Controlled Migraine Trialsa
Adverse Event Type | Percent of Patients Reporting
Adverse Event Type | Placebo; (N = 309) | IMITREX; 25 mg; (N = 417) | IMITREX; 50 mg; (N = 771) | IMITREX; 100 mg; (N = 437)
Atypical sensations | 4% | 5% | 6% | 6%
Paresthesia (all types) | 2% | 3% | 5% | 3%
Sensation warm/cold | 2% | 3% | 2% | 3%
Pain and other pressure sensations | 4% | 6% | 6% | 8%
Chest - pain/tightness/pressure and/or heaviness | 1% | 1% | 2% | 2%
Neck/throat/jaw - pain/ tightness/pressure | <1% | <1% | 2% | 3%
Pain - location specified | 1% | 2% | 1% | 1%
Other - pressure/tightness/ heaviness | 2% | 1% | 1% | 3%
Neurological
Vertigo | <1% | <1% | <1% | 2%
Other
Malaise/fatigue | <1% | 2% | 2% | 3%

aEvents that occurred at a frequency of 2% or more in the group treated with IMITREX Tablets and that occurred more frequently in that group than the placebo group.

Other events that occurred in more than 1% of patients receiving IMITREX Tablets and at least as often on placebo included nausea and/or vomiting, migraine, headache, hyposalivation, dizziness, and drowsiness/sleepiness.

IMITREX Tablets are generally well tolerated. Across all doses, most adverse reactions were mild and transient and did not lead to long-lasting effects. The incidence of adverse events in controlled clinical trials was not affected by gender or age of the patients. There were insufficient data to assess the impact of race on the incidence of adverse events.

Other Events Observed in Association With the Administration of IMITREX Tablets

In the paragraphs that follow, the frequencies of less commonly reported adverse clinical events are presented. Because the reports include events observed in open and uncontrolled studies, the role of IMITREX Tablets in their causation cannot be reliably determined. Furthermore, variability associated with adverse event reporting, the terminology used to describe adverse events, etc., limit the value of quantitative frequency estimates provided. Event frequencies are calculated as the number of patients who used IMITREX Tablets (25, 50, or 100 mg) and reported an event divided by the total number of patients (N = 6,348) exposed to IMITREX Tablets. All reported events are included except those already listed in the previous table, those too general to be informative, and those not reasonably associated with the use of the drug. Events are further classified within body system categories and enumerated in order of decreasing frequency using the following definitions: frequent adverse events are defined as those occurring in at least 1/100 patients, infrequent adverse events are those occurring in 1/100 to 1/1,000 patients, and rare adverse events are those occurring in fewer than 1/1,000 patients.

Atypical Sensations: Frequent were burning sensation and numbness. Infrequent was tight feeling in head. Rare were dysesthesia.

Cardiovascular: Frequent were palpitations, syncope, decreased blood pressure, and increased blood pressure. Infrequent were arrhythmia, changes in ECG, hypertension, hypotension, pallor, pulsating sensations, and tachycardia. Rare were angina, atherosclerosis, bradycardia, cerebral ischemia, cerebrovascular lesion, heart block, peripheral cyanosis, thrombosis, transient myocardial ischemia, and vasodilation.

Ear, Nose, and Throat: Frequent were sinusitis, tinnitus; allergic rhinitis; upper respiratory inflammation; ear, nose, and throat hemorrhage; external otitis; hearing loss; nasal inflammation; and sensitivity to noise. Infrequent were hearing disturbances and otalgia. Rare was feeling of fullness in the ear(s).

Endocrine and Metabolic: Infrequent was thirst. Rare were elevated thyrotropin stimulating hormone (TSH) levels; galactorrhea; hyperglycemia; hypoglycemia; hypothyroidism; polydipsia; weight gain; weight loss; endocrine cysts, lumps, and masses; and fluid disturbances.

Eye: Rare were disorders of sclera, mydriasis, blindness and low vision, visual disturbances, eye edema and swelling, eye irritation and itching, accommodation disorders, external ocular muscle disorders, eye hemorrhage, eye pain, and keratitis and conjunctivitis.

Gastrointestinal: Frequent were diarrhea and gastric symptoms. Infrequent were constipation, dysphagia, and gastroesophageal reflux. Rare were gastrointestinal bleeding, hematemesis, melena, peptic ulcer, gastrointestinal pain, dyspeptic symptoms, dental pain, feelings of gastrointestinal pressure, gastritis, gastroenteritis, hypersalivation, abdominal distention, oral itching and irritation, salivary gland swelling, and swallowing disorders.

Hematological Disorders: Rare was anemia.

Musculoskeletal: Frequent was myalgia. Infrequent was muscle cramps. Rare were tetany; muscle atrophy, weakness, and tiredness; arthralgia and articular rheumatitis; acquired musculoskeletal deformity; muscle stiffness, tightness, and rigidity; and musculoskeletal inflammation.

Neurological: Frequent were phonophobia and photophobia. Infrequent were confusion, depression, difficulty concentrating, disturbance of smell, dysarthria, euphoria, facial pain, heat sensitivity, incoordination, lacrimation, monoplegia, sleep disturbance, shivering, syncope, and tremor. Rare were aggressiveness, apathy, bradylogia, cluster headache, convulsions, decreased appetite, drug abuse, dystonic reaction, facial paralysis, hallucinations, hunger, hyperesthesia, hysteria, increased alertness, memory disturbance, neuralgia, paralysis, personality change, phobia, radiculopathy, rigidity, suicide, twitching, agitation, anxiety, depressive disorders, detachment, motor dysfunction, neurotic disorders, psychomotor disorders, taste disturbances, and raised intracranial pressure.

Respiratory: Frequent was dyspnea. Infrequent was asthma. Rare were hiccoughs, breathing disorders, cough, and bronchitis.

Skin: Frequent was sweating. Infrequent were erythema, pruritus, rash, and skin tenderness. Rare were dry/scaly skin, tightness of skin, wrinkling of skin, eczema, seborrheic dermatitis, and skin nodules.

Breasts: Infrequent was tenderness. Rare were nipple discharge; breast swelling; cysts, lumps, and masses of breasts; and primary malignant breast neoplasm.

Urogenital: Infrequent were dysmenorrhea, increased urination, and intermenstrual bleeding. Rare were abortion and hematuria, urinary frequency, bladder inflammation, micturition disorders, urethritis, urinary infections, menstruation symptoms, abnormal menstrual cycle, inflammation of fallopian tubes, and menstrual cycle symptoms.

Miscellaneous: Frequent was hypersensitivity. Infrequent were fever, fluid retention, and overdose. Rare were edema, hematoma, lymphadenopathy, speech disturbance, voice disturbances, contusions.

Other Events Observed in the Clinical Development of IMITREX

The following adverse events occurred in clinical trials with IMITREX Injection and IMITREX Nasal Spray. Because the reports include events observed in open and uncontrolled studies, the role of IMITREX in their causation cannot be reliably determined. All reported events are included except those already listed, those too general to be informative, and those not reasonably associated with the use of the drug.

Atypical Sensations: Feeling strange, prickling sensation, tingling, and hot sensation.

Cardiovascular: Abdominal aortic aneurysm, abnormal pulse, flushing, phlebitis, Raynaud syndrome, and various transient ECG changes (nonspecific ST or T wave changes, prolongation of PR or QTc intervals, sinus arrhythmia, nonsustained ventricular premature beats, isolated junctional ectopic beats, atrial ectopic beats, delayed activation of the right ventricle).

Chest Symptoms: Chest discomfort.

Endocrine and Metabolic: Dehydration.

Ear, Nose, and Throat: Disorder/discomfort nasal cavity and sinuses, ear infection, Meniere disease, and throat discomfort.

Eye: Vision alterations.

Gastrointestinal: Abdominal discomfort, colitis, disturbance of liver function tests, flatulence/eructation, gallstones, intestinal obstruction, pancreatitis, and retching.

Injection Site Reaction

Miscellaneous: Difficulty in walking, hypersensitivity to various agents, jaw discomfort, miscellaneous laboratory abnormalities, “serotonin agonist effect,” swelling of the extremities, and swelling of the face.

Mouth and Teeth: Disorder of mouth and tongue (e.g., burning of tongue, numbness of tongue, dry mouth).

Musculoskeletal: Arthritis, backache, intervertebral disc disorder, neck pain/stiffness, need to flex calf muscles, and various joint disturbances (pain, stiffness, swelling, ache).

Neurological: Bad/unusual taste, chills, diplegia, disturbance of emotions, sedation, globus hystericus, intoxication, myoclonia, neoplasm of pituitary, relaxation, sensation of lightness, simultaneous hot and cold sensations, stinging sensations, stress, tickling sensations, transient hemiplegia, and yawning.

Respiratory: Influenza and diseases of the lower respiratory tract and lower respiratory tract infection.

Skin: Skin eruption, herpes, and peeling of the skin.

Urogenital: Disorder of breasts, endometriosis, and renal calculus.

Postmarketing Experience (Reports for Subcutaneous or Oral Sumatriptan)

The following section enumerates potentially important adverse events that have occurred in clinical practice and that have been reported spontaneously to various surveillance systems. The events enumerated represent reports arising from both domestic and nondomestic use of oral or subcutaneous dosage forms of sumatriptan. The events enumerated include all except those already listed in the ADVERSE REACTIONS section above or those too general to be informative. Because the reports cite events reported spontaneously from worldwide postmarketing experience, frequency of events and the role of sumatriptan in their causation cannot be reliably determined. It is assumed, however, that systemic reactions following sumatriptan use are likely to be similar regardless of route of administration.

Blood: Hemolytic anemia, pancytopenia, thrombocytopenia.

Cardiovascular: Atrial fibrillation, cardiomyopathy, colonic ischemia (see WARNINGS), Prinzmetal variant angina, pulmonary embolism, shock, thrombophlebitis.

Ear, Nose, and Throat: Deafness.

Eye: Ischemic optic neuropathy, retinal artery occlusion, retinal vein thrombosis, loss of vision.

Gastrointestinal: Ischemic colitis with rectal bleeding (see WARNINGS), xerostomia.

Hepatic: Elevated liver function tests.

Neurological: Central nervous system vasculitis, cerebrovascular accident, dysphasia, serotonin syndrome, subarachnoid hemorrhage.

Non-Site Specific: Angioneurotic edema, cyanosis, death (see WARNINGS), temporal arteritis.

Psychiatry: Panic disorder.

Respiratory: Bronchospasm in patients with and without a history of asthma.

Skin: Exacerbation of sunburn, hypersensitivity reactions (allergic vasculitis, erythema, pruritus, rash, shortness of breath, urticaria; in addition, severe anaphylaxis/anaphylactoid reactions have been reported [see WARNINGS]), photosensitivity.

Urogenital: Acute renal failure.

DRUG ABUSE AND DEPENDENCE

One clinical study with IMITREX Injection enrolling 12 patients with a history of substance abuse failed to induce subjective behavior and/or physiologic response ordinarily associated with drugs that have an established potential for abuse.

OVERDOSAGE

Patients (N = 670) have received single oral doses of 140 to 300 mg without significant adverse effects. Volunteers (N = 174) have received single oral doses of 140 to 400 mg without serious adverse events.

Overdose in animals has been fatal and has been heralded by convulsions, tremor, paralysis, inactivity, ptosis, erythema of the extremities, abnormal respiration, cyanosis, ataxia, mydriasis, salivation, and lacrimation. The elimination half-life of sumatriptan is approximately 2.5 hours (see CLINICAL PHARMACOLOGY), and therefore monitoring of patients after overdose with IMITREX Tablets should continue for at least 12 hours or while symptoms or signs persist.

It is unknown what effect hemodialysis or peritoneal dialysis has on the serum concentrations of sumatriptan.

DOSAGE AND ADMINISTRATION

In controlled clinical trials, single doses of 25, 50, or 100 mg of IMITREX Tablets were effective for the acute treatment of migraine in adults. There is evidence that doses of 50 and 100 mg may provide a greater effect than 25 mg (see CLINICAL TRIALS). There is also evidence that doses of 100 mg do not provide a greater effect than 50 mg. Individuals may vary in response to doses of IMITREX Tablets. The choice of dose should therefore be made on an individual basis, weighing the possible benefit of a higher dose with the potential for a greater risk of adverse events.

If the headache returns or the patient has a partial response to the initial dose, the dose may be repeated after 2 hours, not to exceed a total daily dose of 200 mg. If a headache returns following an initial treatment with IMITREX Injection, additional single IMITREX Tablets (up to 100 mg/day) may be given with an interval of at least 2 hours between tablet doses. The safety of treating an average of more than 4 headaches in a 30-day period has not been established.

Because of the potential of MAO-A inhibitors to cause unpredictable elevations in the bioavailability of oral sumatriptan, their combined use is contraindicated (see CONTRAINDICATIONS).

Hepatic disease/functional impairment may also cause unpredictable elevations in the bioavailability of orally administered sumatriptan. Consequently, if treatment is deemed advisable in the presence of liver disease, the maximum single dose should in general not exceed 50 mg (see CLINICAL PHARMACOLOGY for the basis of this recommendation).

HOW SUPPLIED

IMITREX Tablets, 100 mg of sumatriptan (base) as the succinate.

IMITREX Tablets, 100 mg, are pink, triangular-shaped, film-coated tablets debossed with “IMITREX 100” on one side and a chevron shape (^) on the other in blister packs of 9 tablets (NDC 54868-5118-0).

Store between 36° and 86°F (2° and 30°C).

ANIMAL TOXICOLOGY

Corneal Opacities

Dogs receiving oral sumatriptan developed corneal opacities and defects in the corneal epithelium. Corneal opacities were seen at the lowest dosage tested, 2 mg/kg/day, and were present after 1 month of treatment. Defects in the corneal epithelium were noted in a 60-week study. Earlier examinations for these toxicities were not conducted and no-effect doses were not established; however, the relative exposure at the lowest dose tested was approximately 5 times the human exposure after a 100-mg oral dose. There is evidence of alterations in corneal appearance on the first day of intranasal dosing to dogs. Changes were noted at the lowest dose tested, which was approximately one half the maximum single human oral dose of 100 mg on a mg/m^2 basis.

GlaxoSmithKline

Research Triangle Park, NC 27709

©2012, GlaxoSmithKline. All rights reserved.

March 2012

IMT:3PI

Additional barcode labeling by:

Physicians Total Care, Inc.

Tulsa, Oklahoma 74146

PATIENT INFORMATION

The following wording is contained in a separate leaflet provided for patients.

Patient Information

IMITREX® (IM-i-trex)

(sumatriptansuccinate)

Tablets

Read this Patient Information before you start taking IMITREX and each time you get a refill. There may be new information. This information does not take the place of talking with your healthcare provider about your medical condition or treatment.

What is the most important information I should know about IMITREX?

IMITREX can cause serious side effects, including:

Heart attack and other heart problems. Heart problems may lead to death.

Stop taking IMITREX and get emergency medical help right away if you have any of the following symptoms of a heart attack:

- discomfort in the center of your chest that lasts for more than a few minutes, or that goes away and comes back
- chest pain or chest discomfort that feels like heavy pressure, squeezing, or fullness
- pain or discomfort in your arms, back, neck, jaw, or stomach
- shortness of breath with or without chest discomfort
- breaking out in a cold sweat
- nausea or vomiting
- feeling lightheaded

IMITREX is not for people with risk factors for heart disease unless a heart exam is done and shows no problem. You have a higher risk for heart disease if you:

- have high blood pressure
- have high cholesterol levels
- smoke
- are overweight
- have diabetes
- have a family history of heart disease
- are a female who has gone through menopause
- are a male over age 40

Serotonin syndrome. Serotonin syndrome is a serious and life-threatening problem that can happen in people taking IMITREX, especially if IMITREX is used with anti-depressant medicines called selective serotonin reuptake inhibitors (SSRIs) or selective norepinephrine reuptake inhibitors (SNRIs).

Ask your healthcare provider or pharmacist for a list of these medicines if you are not sure.

Call your healthcare provider right away if you have any of the following symptoms of serotonin syndrome:

- mental changes such as seeing things that are not there (hallucinations), agitation, or coma
- fast heartbeat
- changes in blood pressure
- high body temperature
- tight muscles
- trouble walking
- nausea, vomiting, or diarrhea

What is IMITREX?

IMITREX is a prescription medicine used to treat acute migraine headaches with or without aura in adults.

IMITREX is not used to prevent or decrease the number of migraine headaches you have.

IMITREX is not used to treat other types of headaches such as hemiplegic (that make you unable to move on one side of your body) or basilar migraines (rare form of migraine with aura).

It is not known if IMITREX is safe and effective to treat cluster headaches.

It is not known if IMITREX is safe and effective in children under 18 years of age.

Who should not take IMITREX?

Do not take IMITREX if you have:

- heart problems or a history of heart problems
- narrowing of blood vessels to your legs, arms, stomach, or kidney (peripheral vascular disease)
- uncontrolled high blood pressure
- severe liver problems
- hemiplegic migraines or basilar migraines. If you are not sure if you have these types of migraines, ask your healthcare provider.
- had a stroke, transient ischemic attacks (TIAs), or problems with your blood circulation
- taken any of the following medicines in the last 24 hours:
  - almotriptan (AXERT®)
  - eletriptan (RELPAX®)
  - frovatriptan (FROVA®)
  - naratriptan (AMERGE®)
  - rizatriptan (MAXALT®, MAXALT-MLT®)
  - sumatriptan and naproxen (TREXIMET®)
  - ergotamines (CAFERGOT®, ERGOMAR®, MIGERGOT®)
  - dihydroergotamine (D.H.E. 45®, MIGRANAL®)

Ask your doctor if you are not sure if your medicine is listed above.

- an allergy to sumatriptan or any of the ingredients in IMITREX. See the end of this leaflet for a complete list of ingredients in IMITREX.

What should I tell my healthcare provider before taking IMITREX?

Before you take IMITREX, tell your healthcare provider about all of your medical conditions, including if you:

- have high blood pressure
- have high cholesterol
- have diabetes
- smoke
- are overweight
- are a female who has gone through menopause
- have heart disease or a family history of heart disease or stroke
- have kidney problems
- have liver problems
- have had epilepsy or seizures
- are not using effective birth control
- are pregnant or plan to become pregnant. It is not known if IMITREX will harm your unborn baby.
- become pregnant while taking IMITREX
- are breastfeeding or plan to breastfeed. IMITREX passes into your breast milk and may harm your baby. Talk with your healthcare provider about the best way to feed your baby if you take IMITREX.

Tell your healthcare provider about all the medicines you take, including prescription and nonprescription medicines, vitamins, and herbal supplements.

IMITREX and other medicines may affect each other, causing side effects.

Especially tell your healthcare provider if you take anti-depressant medicines called:

- selective serotonin reuptake inhibitors (SSRIs)
- serotonin norepinephrine reuptake inhibitors (SNRIs)
- monoamine oxidase inhibitors (MAOIs)

Ask your healthcare provider or pharmacist for a list of these medicines if you are not sure.

Know the medicines you take. Keep a list of them to show your healthcare provider or pharmacist when you get a new medicine.

How should I take IMITREX?

- Certain people should take their first dose of IMITREX in their healthcare provider’s office or in another medical setting. Ask your healthcare provider if you should take your first dose in a medical setting.
- Take IMITREX exactly as your healthcare provider tells you to take it.
- Your healthcare provider may change your dose. Do not change your dose without first talking to your healthcare provider.
- Take IMITREX with water or other liquids.
- If you do not get any relief after your first IMITREX tablet, do not take a second tablet without first talking with your healthcare provider.
- If your headache comes back or you only get some relief from your headache, you can take a second tablet 2 hours after the first tablet.
- Do not take more than a total of 200 mg of IMITREX tablets in a 24‑hour period.
- Some people who take too many IMITREX tablets may have worse headaches (medication overuse headache). If your headaches get worse, your healthcare provider may decide to stop your treatment with IMITREX.
- If you take too much IMITREX, call your healthcare provider or go to the nearest hospital emergency room right away.
- You should write down when you have headaches and when you take IMITREX so you can talk with your healthcare provider about how IMITREX is working for you.

What should I avoid while taking IMITREX?

IMITREX can cause dizziness, weakness, or drowsiness. If you have these symptoms, do not drive a car, use machinery, or do anything where you need to be alert.

What are the possible side effects of IMITREX?

IMITREX may cause serious side effects. See “What is the most important information I should know about IMITREX?”

These serious side effects include:

- changes in color or sensation in your fingers and toes (Raynaud’s syndrome)
- stomach and intestinal problems (gastrointestinal and colonic ischemic events). Symptoms of gastrointestinal and colonic ischemic events include:
  - sudden or severe stomach pain
  - stomach pain after meals
  - weight loss
  - nausea or vomiting
  - constipation or diarrhea
  - bloody diarrhea
  - fever
- problems with blood circulation to your legs and feet (peripheral vascular ischemia). Symptoms of peripheral vascular ischemia include:
  - cramping and pain in your legs or hips
  - feeling of heaviness or tightness in your leg muscles
  - burning or aching pain in your feet or toes while resting
  - numbness, tingling, or weakness in your legs
  - cold feeling or color changes in 1 or both legs or feet
- shortness of breath or wheezing
- hives (itchy bumps); swelling of your tongue, mouth, or throat

The most common side effects of IMITREX include:

- tingling or numbness in your fingers or toes
- dizziness
- warm, hot, burning feeling to your face (flushing)
- feeling weak, drowsy, or tired

Tell your healthcare provider if you have any side effect that bothers you or that does not go away.

These are not all the possible side effects of IMITREX. For more information, ask your healthcare provider or pharmacist.

Call your doctor for medical advice about side effects. You may report side effects to FDA at 1-800-FDA-1088.

How should I store IMITREX Tablets?

Store IMITREX between 36°F to 86°F (2°C to 30°C).

Keep IMITREX and all medicines out of the reach of children.

General information about the safe and effective use of IMITREX.

Medicines are sometimes prescribed for purposes other than those listed in Patient Information leaflets. Do not use IMITREX for a condition for which it was not prescribed. Do not give IMITREX to other people, even if they have the same symptoms you have. It may harm them.

This Patient Information leaflet summarizes the most important information about IMITREX. If you would like more information, talk with your healthcare provider. You can ask your healthcare provider or pharmacist for information about IMITREX that is written for healthcare professionals.

For more information, go to www.gsk.com or call 1-888-825-5249.

What are the ingredients in IMITREX Tablets?

Active ingredient: sumatriptan succinate

Inactive ingredients: croscarmellose sodium, dibasic calcium phosphate, magnesium stearate, microcrystalline cellulose, and sodium bicarbonate

100‑mg tablets also contain hypromellose, iron oxide, titanium dioxide, and triacetin.

imitrex, AMERGE, and TREXIMET are registered trademarks of GlaxoSmithKline. The other brands listed are trademarks of their respective owners and are not trademarks of GlaxoSmithKline. The makers of these brands are not affiliated with and do not endorse GlaxoSmithKline or its products.

This Patient Information has been approved by the U.S. Food and Drug Administration.

GlaxoSmithKline

Research Triangle Park, NC 27709

©2012, GlaxoSmithKline. All rights reserved.

March 2012

IMT:3PIL

Principal Display Panel

NDC 54868-3777-0

IMITREX®

(SUMATRIPTAN SUCCINATE)

TABLETS

25 mg

9 Tablets

Rx only

Each tablet contains sumatriptan succinate equivalent to 25 mg of sumatriptan.

Do not use if package is torn or broken or if you receive fewer tablets than your doctor prescribed.

See prescribing information for dosage information.

Store between 36o and 86oF (2o and 30oC).

Principal Display Panel

NDC 54868-3852-0

IMITREX®

(SUMATRIPTAN SUCCINATE)

TABLETS

50 mg

9 Tablets

Rx only

Each tablet contains sumatriptan succinate equivalent to 50 mg of sumatriptan.

Do not use if package is torn or broken or if you receive fewer tablets than your doctor prescribed.

See prescribing information for dosage information.

Store between 36o and 86oF (2o and 30oC).

Prinicpal Display Panel

NDC 54868-5118-0

IMITREX®

(SUMATRIPTAN SUCCINATE)

TABLETS

100 mg

9 Tablets

Rx only

Each tablet contains sumatriptan succinate equivalent to 100 mg of sumatriptan.

Do not use if package is torn or broken or if you receive fewer tablets than your doctor prescribed.

See prescribing information for dosage information.

Store between 36o and 86oF (2o and 30oC).